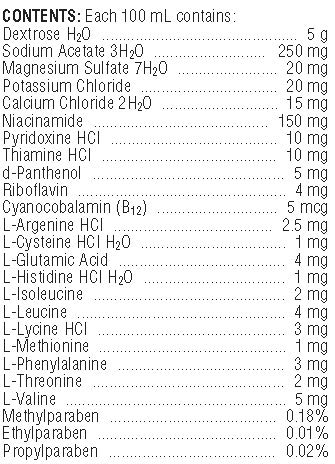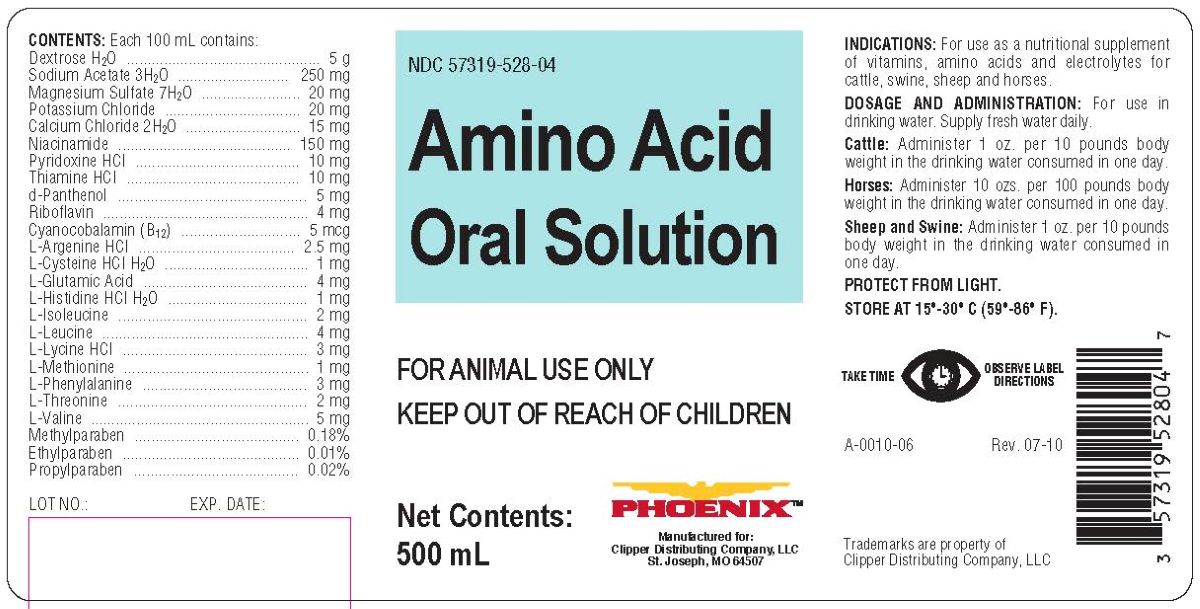 DRUG LABEL: AMINO ACID 
NDC: 57319-528 | Form: SOLUTION
Manufacturer: Clipper Distributing Company, LLC
Category: animal | Type: OTC ANIMAL DRUG LABEL
Date: 20240605

ACTIVE INGREDIENTS: DEXTROSE MONOHYDRATE 5000 mg/100 mL; CALCIUM CHLORIDE ANHYDROUS 15 mg/100 mL; MAGNESIUM SULFATE HEPTAHYDRATE 20  mg/100 mL; POTASSIUM CHLORIDE 20 mg/100 mL; SODIUM ACETATE ANHYDROUS 250 mg/100 mL
INACTIVE INGREDIENTS: VALINE

AMINO ACID ORAL SOLUTION

INDICATIONS AND USAGE

FOR ANIMAL USE ONLY

KEEP OUT OF REACH OF CHILDREN

INDICATIONS

For use as a nutritional supplement of vitamins, amino acids and electrolytes for cattle, swine, sheep and horses.

DOSAGE AND ADMINISTRATION

For use in drinking water. Supply fresh water daily.

Cattle: Administer 1 oz. per 10 pounds body weight in the drinking water consumed in one day.

Horses: Administer 10 ozs. per 100 pounds body weight in the drinking water consumed in one day.

Sheep and Swine: Administer 1 oz. per 10 pounds body weight i the drinking water consume in one day.

STORAGE AND HANDLING

PROTECT FROM LIGHT.

STORE AT 15o-30oC (59o-86oF).